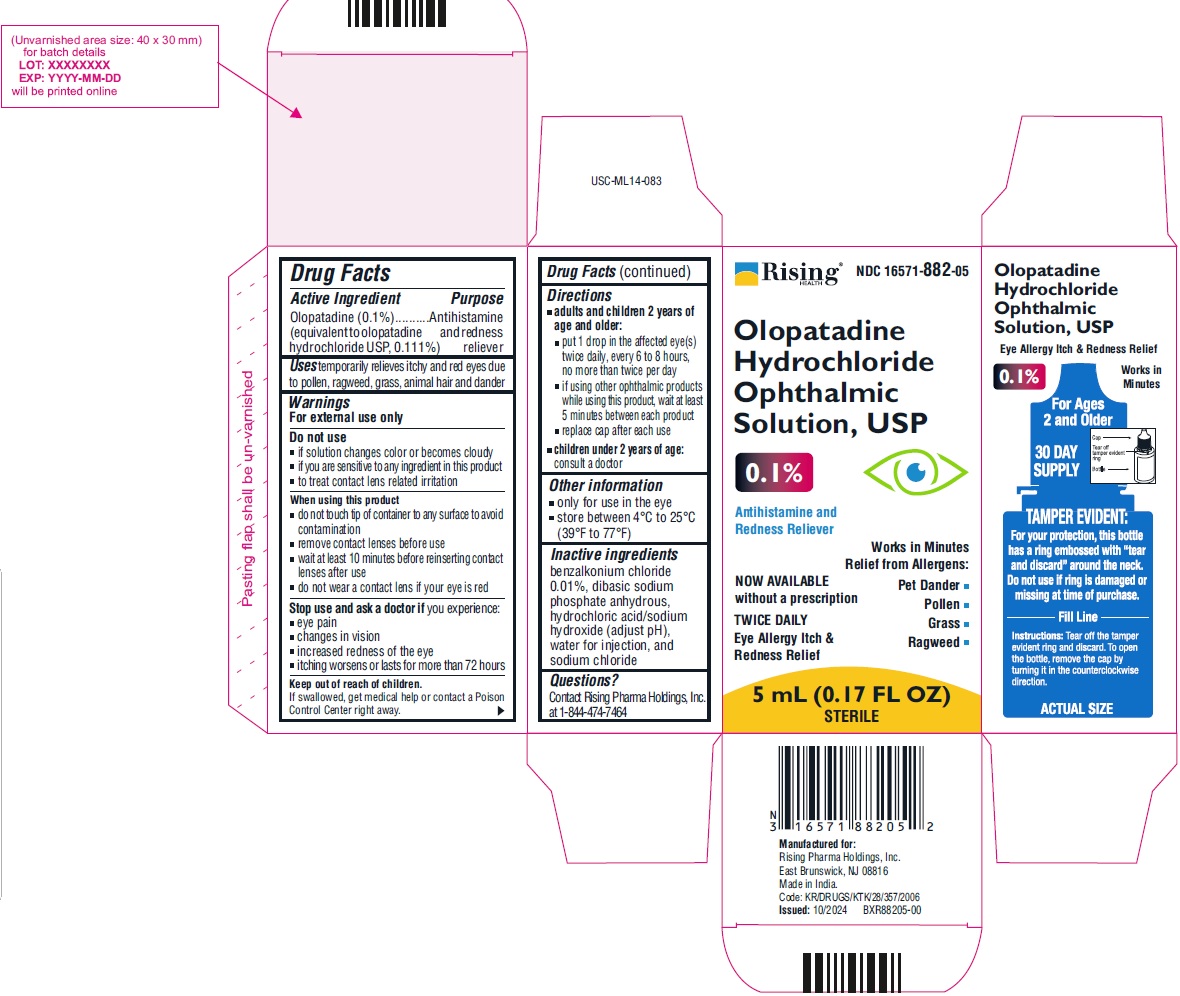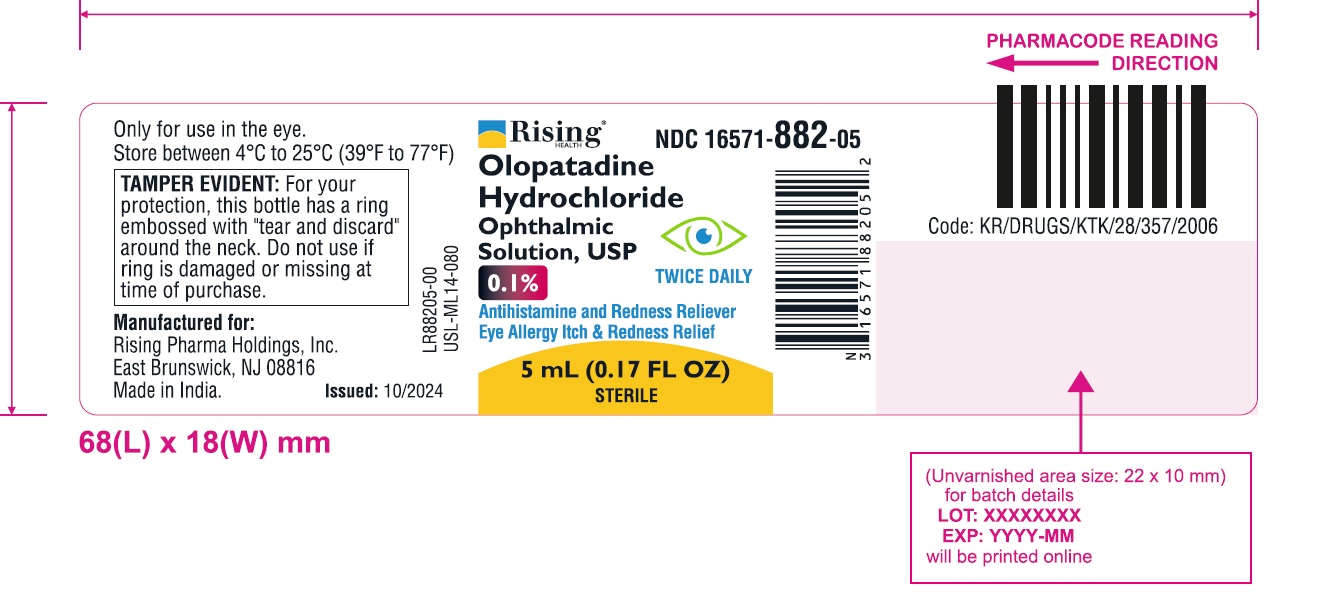 DRUG LABEL: olopatadine hydrochloride
NDC: 16571-882 | Form: SOLUTION
Manufacturer: Rising Pharma Holdings, Inc.
Category: otc | Type: Human OTC Drug Label
Date: 20250404

ACTIVE INGREDIENTS: OLOPATADINE HYDROCHLORIDE 1 mg/1 mL
INACTIVE INGREDIENTS: BENZALKONIUM CHLORIDE; SODIUM PHOSPHATE, DIBASIC, ANHYDROUS; SODIUM CHLORIDE; HYDROCHLORIC ACID; SODIUM HYDROXIDE; WATER

Olopatadine Hydrochloride Ophthalmic Solution, USP 0.1%

ACTIVE INGREDIENT(S)

Olopatadine (0.1%) (equivalent to olopatadine hydrochloride USP, 0.111%)

PURPOSE

Antihistamine and redness reliever

USE(S)

temporarily relieves itchy and red eyes due to pollen, ragweed, grass, animal hair and dander

WARNINGS

For external use only

DO NOT USE

▪ if solution changes color or becomes cloudy
▪ if you are sensitive to any ingredient in this product
▪ to treat contact lens related irritation

WHEN USING THIS PRODUCT

▪ do not touch tip of container to any surface to avoid contamination
▪ remove contact lenses before use
▪ wait at least 10 minutes before reinserting contact lenses after use
▪ do not wear a contact lens if your eye is red

STOP USE AND ASK DOCTOR IF

you experience:
▪ eye pain
▪ changes in vision
▪ increased redness of the eye
▪ itching worsens or lasts for more than 72 hours

KEEP OUT OF REACH OF CHILDREN

If swallowed, get medical help or contact a Poison Control Center right away.

DIRECTIONS

▪ adults and children 2 years of age and older:
▪ put 1 drop in the affected eye(s) twice daily, every 6 to 8 hours, no more than twice per day
▪ if using other ophthalmic products while using this product, wait at least 5 minutes between each product
▪ replace cap after each use
▪ children under 2 years of age:
consult a doctor

Other information

▪ only for use in the eye
▪ store between 4°C to 25°C (39°F to 77°F)

Inactive ingredients

benzalkonium chloride 0.01%, dibasic sodium phosphate anhydrous, hydrochloric acid/sodium hydroxide (adjust pH), water for injection, and sodium chloride

Questions?

Contact Rising Pharma Holdings, Inc. at 1-844-474-7464

PRINCIPAL DISPLAY PANEL

Rising NDC 16571-882-05
Olopatadine Hydrochloride Ophthalmic Solution, USP 0.1%

Antihistamine and Redness Reliever

NOW AVAILABLE without a prescription
TWICE DAILY

Eye Allergy Itch & Redness Relief

Works in Minutes Relief from Allergens:
•Pet Dander
•Grass
•Pollen
•Ragweed

5 mL (0.17 FL OZ) STERILE

Rising NDC 16571-882-05

Olopatadine Hydrochloride Ophthalmic Solution, USP
0.1%
Antihistamine and Redness Reliever
Eye Allergy Itch & Redness Relief
TWICE DAILY
5 mL (0.17 FL OZ)
STERILE